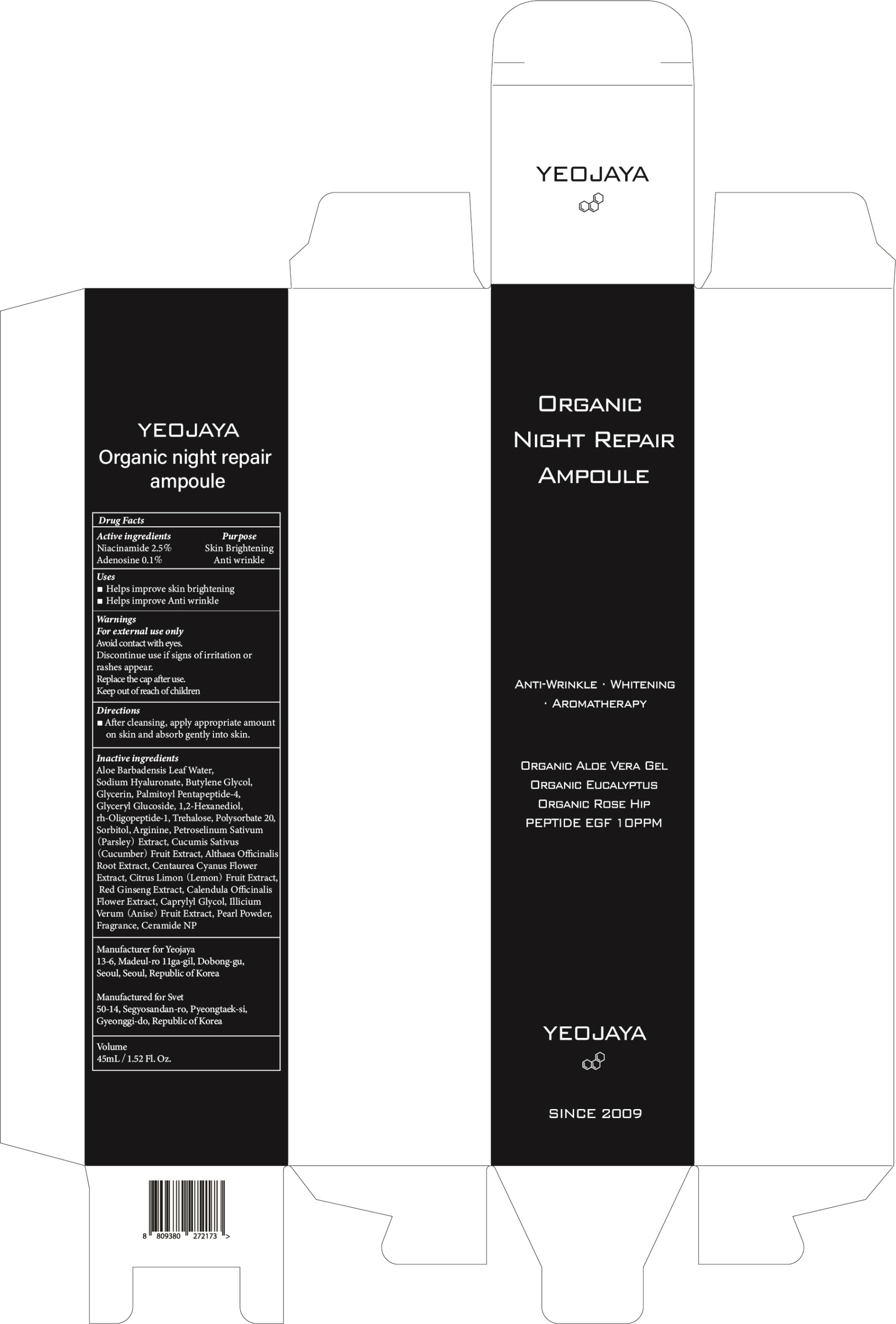 DRUG LABEL: Organic night repair ampoule
NDC: 69142-020 | Form: CREAM
Manufacturer: yeojaya
Category: otc | Type: HUMAN OTC DRUG LABEL
Date: 20180917

ACTIVE INGREDIENTS: Niacinamide 1.12 g/45 mL; Adenosine 0.04 g/45 mL
INACTIVE INGREDIENTS: ALOE VERA LEAF; HYALURONATE SODIUM

ACTIVE INGREDIENT

Active ingredients: Niacinamide 2.5%, Adenosine 0.1%

INACTIVE INGREDIENT

Inactive ingredients:

Aloe Barbadensis Leaf Water, Sodium Hyaluronate, Butylene Glycol, Glycerin, Palmitoyl Pentapeptide-4, Glyceryl Glucoside, 1,2-Hexanediol, rh-Oligopeptide-1, Trehalose, Polysorbate 20, Sorbitol, Arginine, Petroselinum Sativum (Parsley) Extract, Cucumis Sativus (Cucumber) Fruit Extract, Althaea Officinalis Root Extract, Centaurea Cyanus Flower Extract, Citrus Limon (Lemon) Fruit Extract, Red Ginseng Extract, Calendula Officinalis Flower Extract, Caprylyl Glycol, Illicium Verum (Anise) Fruit Extract, Pearl Powder, Fragrance, Ceramide NP

PURPOSE

Purpose: Skin Brightening, Anti wrinkle

WARNINGS

- For external use only

- Avoid contact with eyes.

- Discontinue use if signs of irritation or rashes appear.

- Replace the cap after use.

- Keep out of reach of children

KEEP OUT OF REACH OF CHILDREN

Uses

- Helps improve skin brightening

- Helps improve Anti wrinkle

Directions

- After cleansing, apply appropriate amount on skin and absorb gently into skin.